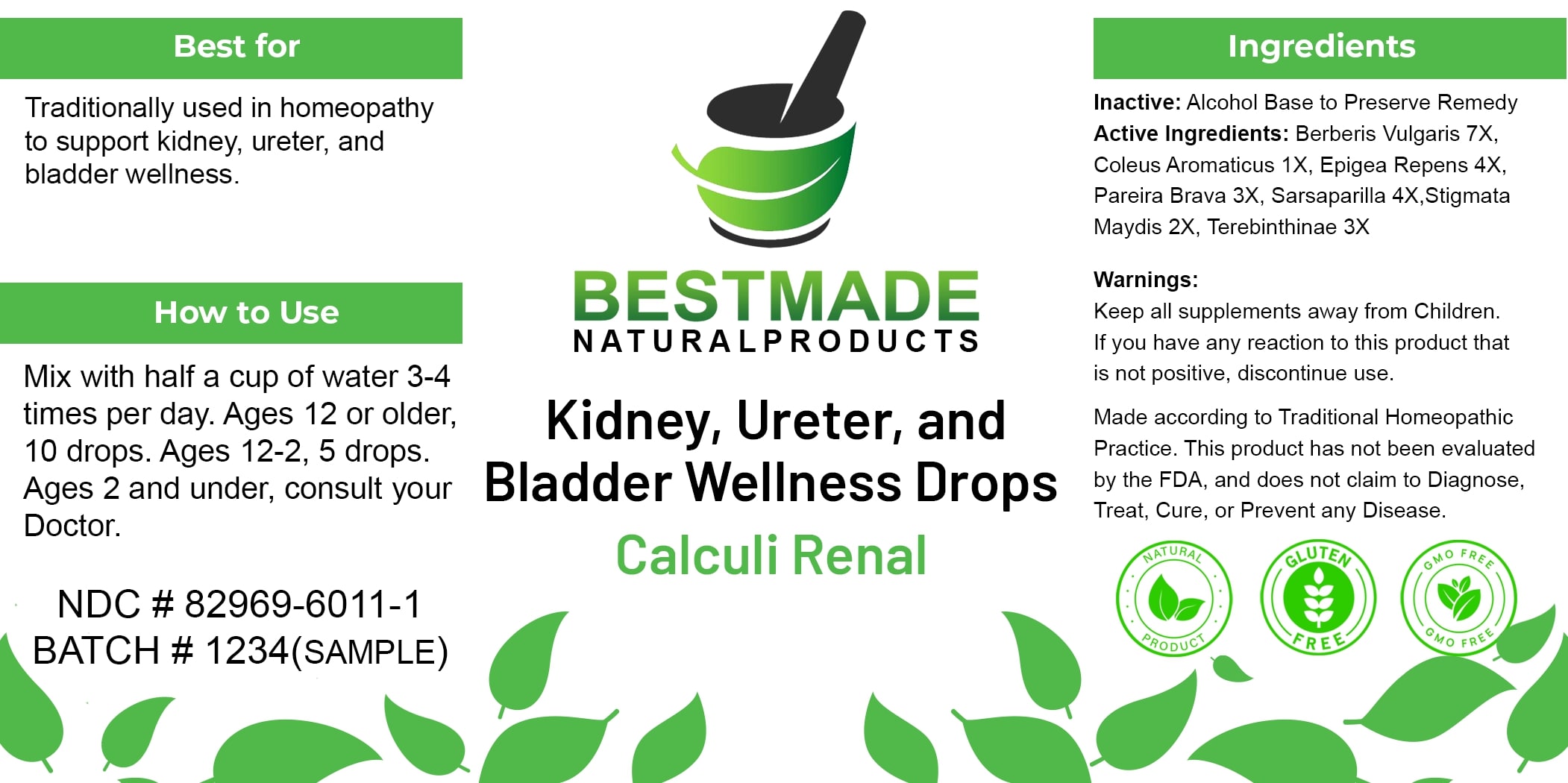 DRUG LABEL: Bestmade Natural Products Calculi Renal
NDC: 82969-6011 | Form: LIQUID
Manufacturer: Bestmade Natural Products
Category: homeopathic | Type: HUMAN OTC DRUG LABEL
Date: 20241218

ACTIVE INGREDIENTS: BERBERIS VULGARIS ROOT BARK 30 [hp_C]/30 [hp_C]; EPIGAEA REPENS 30 [hp_C]/30 [hp_C]; SARSAPARILLA 30 [hp_C]/30 [hp_C]; CORN SILK 30 [hp_C]/30 [hp_C]; TURPENTINE OIL 30 [hp_C]/30 [hp_C]; CHONDRODENDRON TOMENTOSUM ROOT 30 [hp_C]/30 [hp_C]; COLEUS AMBOINICUS WHOLE 30 [hp_C]/30 [hp_C]
INACTIVE INGREDIENTS: ALCOHOL 30 [hp_C]/30 [hp_C]

Calculi Renal

DOSAGE AND ADMINISTRATION

How to Use
Mix with half a cup of water 3-4 times per day. Ages 12 or older, 10 drops. Ages 12-2, 5 drops. Ages 2 and under, consult your Doctor.

INDICATIONS AND USAGE

Best for
Traditionally used in homeopathy to support kidney, ureter, and bladder wellness.

INACTIVE INGREDIENT

Ingredients
Inactive: Alcohol Base to Preserve Remedy

ACTIVE INGREDIENT

Active Ingredients: Berberis Vulgaris 7X, Coleus Aromaticus 1X, Epigea Repens 4X, Pareira Brava 3X, Sarsaparilla 4X, Stigmata Maydis 2X, Terebinthinae 3X

Warnings:
Keep all supplements away from Children.
If you have any reaction to this product that is not positive, discontinue use.

Made according to Traditional Homeopathic Practice. This product has not been evaluated by the FDA, and does not claim to Diagnose, Treat, Cure, or Prevent any Disease.

PURPOSE

Best for
Traditionally used in homeopathy to support kidney, ureter, and bladder wellness.

Warnings:
Keep all supplements away from Children.
If you have any reaction to this product that is not positive, discontinue use.

Made according to Traditional Homeopathic Practice. This product has not been evaluated by the FDA, and does not claim to Diagnose, Treat, Cure, or Prevent any Disease.

Entire package label